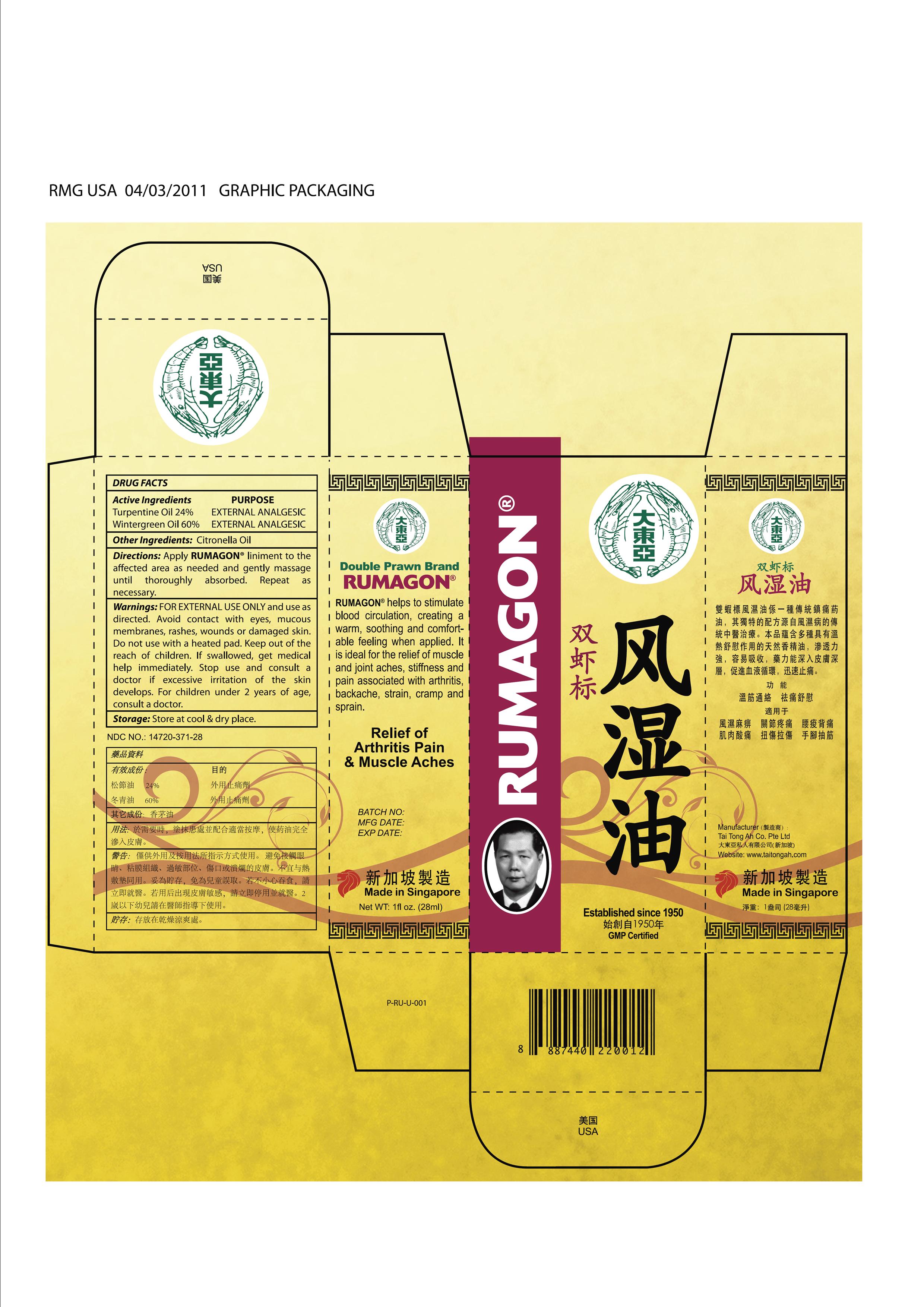 DRUG LABEL: Double Prawn Rumagon
NDC: 14720-371 | Form: LINIMENT
Manufacturer: Tai Tong Ah Co., Pte. Ltd.
Category: otc | Type: HUMAN OTC DRUG LABEL
Date: 20110602

ACTIVE INGREDIENTS: Methyl Salicylate 16.8 mL/28 mL; TURPENTINE 6.72 mL/28 mL
INACTIVE INGREDIENTS: CITRONELLA OIL

DoublePrawnRumagon

Active ingredients : PURPOSE
Methyl salicylate 60% EXTERNAL ANALGESIC
Turpentine 24% EXTERNAL ANALGESIC

Stop use and consult a doctor if excessive irritation of the skin develops.

WARNINGS

Warnings: For external use only and use as directed. Avoid contact with eyes, mucous membranes, rashes, wounds or damaged skin.

KEEP OUT OF REACH OF CHILDREN

Keep out of the reach of children, if swallowed, get medical help immediately.

DOSAGE AND ADMINISTRATION

Directions: Apply RUMAGON liniment to the affected area as needed and gently massage until thoroughly absorbed. Repeat as necessary.

Do not use with a heated pad.

Stop use and consult a doctor if excessive irritation of the skin develops.

INACTIVE INGREDIENT

Other Ingredients: Citronella Oil

STORAGE AND HANDLING

Storage： Store in cool dry place from directly sunlight

INDICATIONS AND USAGE

Relief of Arthritis Pain and Muscle Aches

PURPOSE

provide temporary relief from the muscle / joint aches, stiffness, and pain associated with arthritis, backache, strain, cramp, and sprain.

PACKAGE LABEL

DOUBLE PRAWN RUMAGON LINIMENT
Relief of Arthritis Pain and Muscle Aches
Net WT: 1fl oz. (28ml)
Product of Singapore
RUMAGON liniment is a uniquely developed formula contains natural essential oils that provide temporary relief from the muscle / joint aches, stiffness, and pain associated with arthritis, backache, strain, cramp, and sprain.